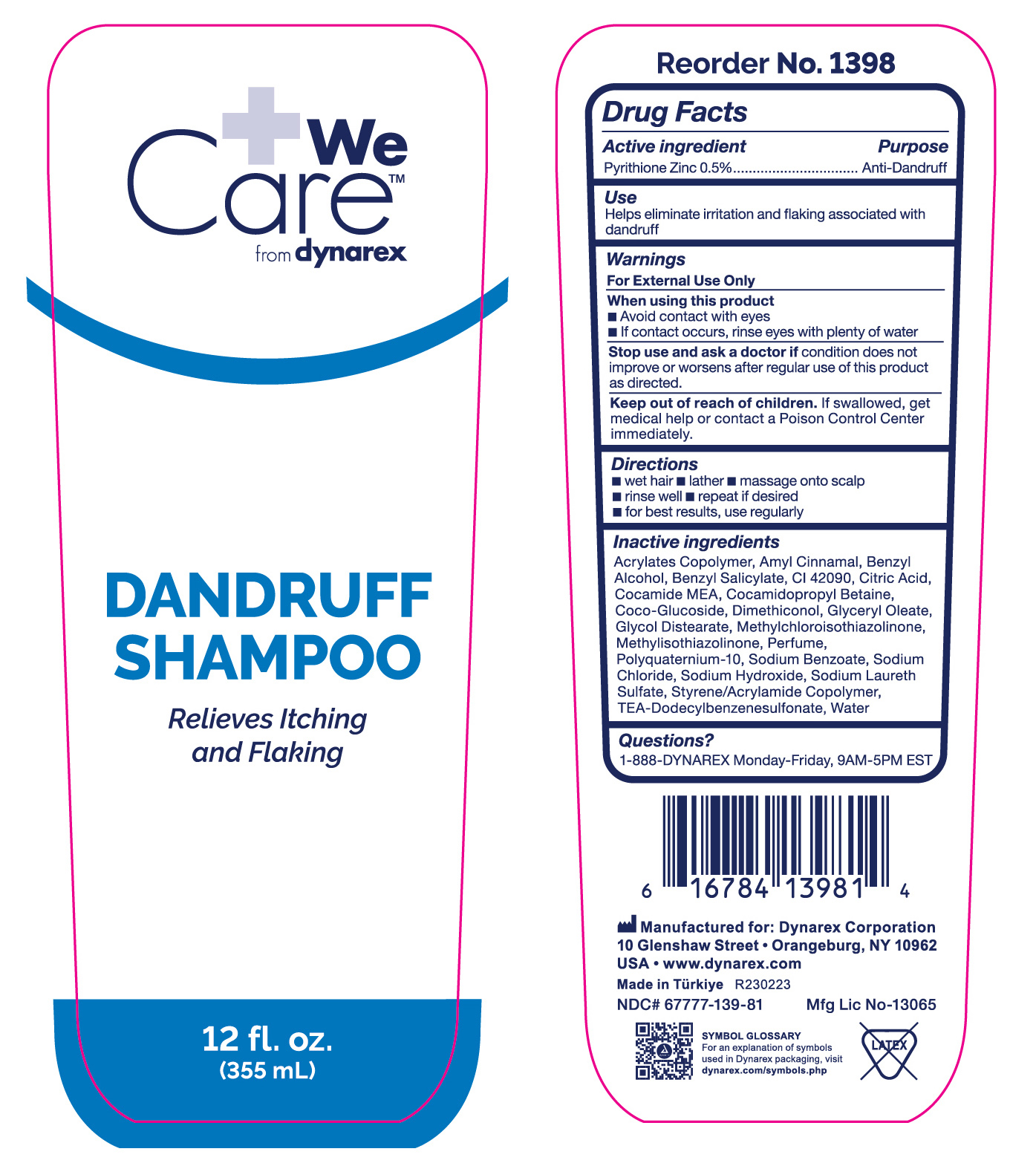 DRUG LABEL: WeCare Anti-Dandruff
NDC: 67777-139 | Form: LIQUID
Manufacturer: Dynarex Corporation
Category: otc | Type: HUMAN OTC DRUG LABEL
Date: 20260128

ACTIVE INGREDIENTS: PYRITHIONE ZINC 5 g/1000 mL
INACTIVE INGREDIENTS: GLYCOL DISTEARATE; GLYCERYL MONOOLEATE; POLYQUATERNIUM-10 (1000 MPA.S AT 2%); TRIETHANOLAMINE DODECYLBENZENESULFONATE; BENZYL ALCOHOL; METHYLCHLOROISOTHIAZOLINONE; BUTYL ACRYLATE/METHYL METHACRYLATE/METHACRYLIC ACID COPOLYMER (18000 MW); SODIUM LAURETH SULFATE; COCO MONOETHANOLAMIDE; SODIUM CHLORIDE; METHYLISOTHIAZOLINONE; .ALPHA.-AMYLCINNAMALDEHYDE; WATER; STYRENE/ACRYLAMIDE COPOLYMER (MW 500000); DIMETHICONOL (2000 CST); CITRIC ACID MONOHYDRATE; SODIUM BENZOATE; BENZYL SALICYLATE; SODIUM HYDROXIDE; FD&C BLUE NO. 1; COCAMIDOPROPYL BETAINE; COCO GLUCOSIDE

1398 Antidandruff Shampoo NDC 67777-139-80

Active ingredient

Pyrithione Zinc 0.5%

Purpose

Anti-Dandruff

Use

Helps eliminate irritation and flaking associated with dandruff

Warnings

For External Use Only

When using this product

- Avoid contact with eyes
- If contact occurs, rinse eyes with plenty of water

Stop use and ask a doctor if

condition does not improve or worsens after regular use of this product as directed.

Keep out of reach of children

If swallowed, get medical help or contact a Poison Control Center immediately.

Directions

- wet hair
- lather
- massage onto scalp
- rinse well
- repeat if desired
- for best results, use regularly

Inactive ingredients

Acrylates Copolymer, Amyl Cinnamal, Benzyl Alcohol, Benzyl Salicylate, CI 42090, Citric Acid, Cocamide MEA, Cocamidopropyl Betaine, Coco-Glucoside, Dimethiconol, Glyceryl Oleate, Glycol Distearate, Methylchloroisothiazolinone, Methylisothiazolinone, Perfume, Polyquaternium-10, Sodium Benzoate, Sodium Chloride, Sodium Hydroxide, Sodium Laureth Sulfate, Styrene/Acrylamide Copolymer, TEA-Dodecylbenzenesulfonate, Water

Label

Dandruff Shampoo